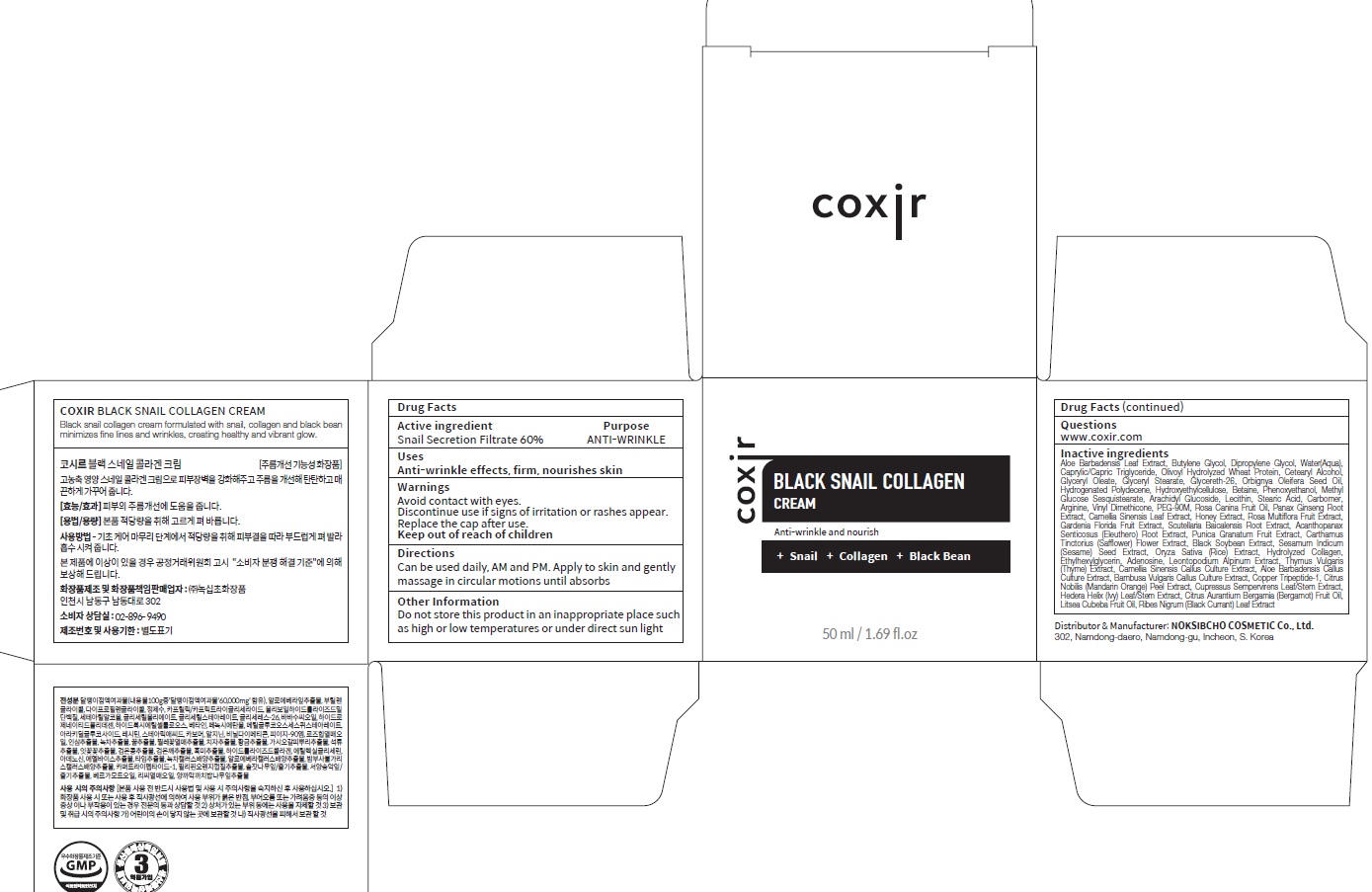 DRUG LABEL: Black Snail CollagenCream
NDC: 73590-0010 | Form: CREAM
Manufacturer: NOKSIBCHO cosmetic Co., Ltd.
Category: otc | Type: HUMAN OTC DRUG LABEL
Date: 20220919

ACTIVE INGREDIENTS: SNAIL, UNSPECIFIED 60 g/100 mL
INACTIVE INGREDIENTS: WATER; BUTYLENE GLYCOL

Drug Facts

ACTIVE INGREDIENT

Snail Secretion Filtrate 60%

INACTIVE INGREDIENTS

Aloe Barbadensis Leaf Extract, Butylene Glycol, Dipropylene Glycol, Water(Aqua), Caprylic/Capric Triglyceride, Olivoyl Hydrolyzed Wheat Protein, Cetearyl Alcohol, Glyceryl Oleate, Glyceryl Stearate, Glycereth-26, Orbignya Oleifera Seed Oil, Hydrogenated Polydecene, Hydroxyethylcellulose,
Betaine, Phenoxyethanol, Methyl Glucose Sesquistearate, Arachidyl Glucoside, Lecithin, Stearic Acid, Carbomer, Arginine, Vinyl Dimethicone, PEG-90M, Rosa Canina Fruit Oil, Panax Ginseng Root Extract, Camellia Sinensis Leaf Extract, Honey Extract, Rosa Multi_ora Fruit Extract, Gardenia Florida Fruit Extract, Scutellaria Baicalensis Root Extract, Acanthopanax Senticosus (Eleuthero) Root Extract, Punica Granatum Fruit Extract,
Carthamus Tinctorius (Saf_ower) Flower Extract, Black Soybean Extract, Sesamum Indicum (Sesame) Seed Extract, Oryza Sativa (Rice) Extract, Hydrolyzed Collagen, Ethylhexylglycerin, Adenosine, Leontopodium Alpinum Extract, Thymus Vulgaris (Thyme) Extract, Camellia Sinensis Callus Culture Extract, Aloe Barbadensis Callus Culture Extract, Bambusa Vulgaris Callus Culture Extract, Copper Tripeptide-1, Citrus Nobilis (Mandarin
Orange) Peel Extract, Cupressus Sempervirens Leaf/Stem Extract, Hedera Helix (Ivy) Leaf/Stem Extract, Citrus Aurantium Bergamia (Bergamot) Fruit Oil, Litsea Cubeba Fruit Oil, Ribes Nigrum (Black Currant) Leaf Extract

PURPOSE

ANTI-WRINKLE

WARNINGS

Avoid contact with eyes.
Discontinue use if signs of irritation or rashes appear.
Replace the cap after use.
Keep out of reach of children

KEEP OUT OF REACH OF CHILDREN

Uses

Anti-wrinkle effects, firm, nourishes skin

Directions

Can be used daily, AM and PM. Apply to skin and gently massage in circular motions until absorbs

Other Information

■ Do not store this product in an inappropriate place such as high or low temperatures or under direct sun light

QUESTIONS

www.coxir.com